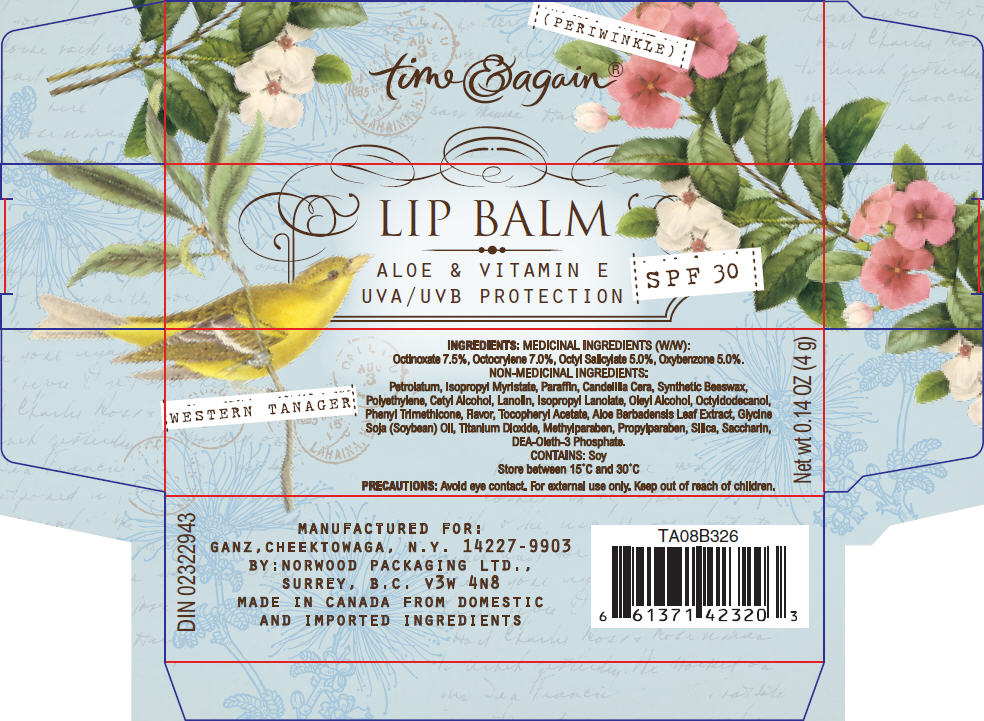 DRUG LABEL: BIRDS GARDEN LIP BALM 
NDC: 55143-010 | Form: STICK
Manufacturer: Norwood Packaging Ltd.
Category: otc | Type: HUMAN OTC DRUG LABEL
Date: 20110321

ACTIVE INGREDIENTS: OCTINOXATE 7.5 g/100 g; OCTOCRYLENE 7 g/100 g; OCTISALATE 5 g/100 g; OXYBENZONE 5 g/100 g
INACTIVE INGREDIENTS: PETROLATUM; ISOPROPYL MYRISTATE; PARAFFIN; CANDELILLA WAX; LOW DENSITY POLYETHYLENE; CETYL ALCOHOL; LANOLIN; OLEYL ALCOHOL; OCTYLDODECANOL; PHENYL TRIMETHICONE; ALPHA-TOCOPHEROL ACETATE; ALOE VERA LEAF; SOYBEAN OIL; TITANIUM DIOXIDE; METHYLPARABEN; PROPYLPARABEN; SILICON DIOXIDE; SACCHARIN

LIP BALM
ALOE & VITAMIN E
UVA / UVB PROTECTION
SPF 30

INGREDIENTS

MEDICINAL INGREDIENTS (W/W)

Octinoxate 7.5%, Octocrylene 7.0%, Octyl Salicylate 5.0%, Oxybenzone 5.0%.

NON-MEDICINAL INGREDIENTS

Petrolatum, Isopropyl Myristate, Paraffin, Candelilla Cera, Synthetic Beeswax, Polyethylene, Cetyl Alcohol, Lanolin, Isopropyl Lanolate, Oleyl Alcohol, Octyldodecanol, Phenyl Trimethicone, Flavor, Tocopheryl Acetate, Aloe Barbadensis Leaf Extract, Glycine Soja (Soybean) Oil, Titanium Dioxide, Methylparaben, Propylparaben, Silica, Saccharin, DEA-Oleth-3 Phosphate.

CONTAINS

Soy

STORAGE AND HANDLING

Store between 15°C and 30°C

PRECAUTIONS

WHEN USING

Avoid eye contact. For external use only.

Keep out of reach of children.

PRINCIPAL DISPLAY PANEL - 4 g Carton

LIP BALM

ALOE & VITAMIN E
UVA / UVB PROTECTION

SPF 30